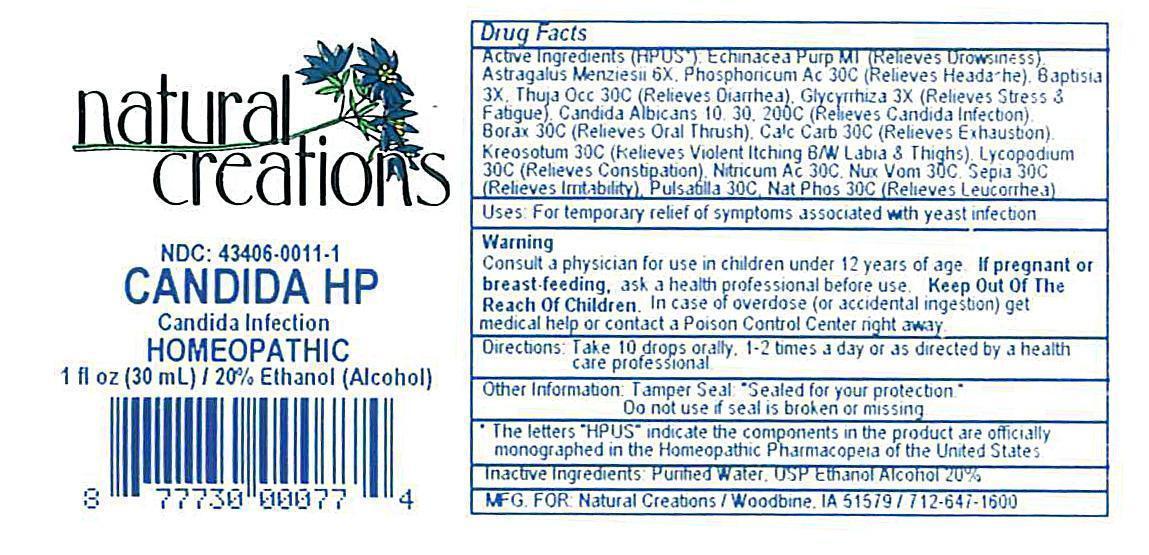 DRUG LABEL: Candida HP
NDC: 43406-0011 | Form: LIQUID
Manufacturer: Natural Creations, Inc.
Category: homeopathic | Type: HUMAN OTC DRUG LABEL
Date: 20121016

ACTIVE INGREDIENTS: ECHINACEA PURPUREA 1 [hp_X]/1 mL; BAPTISIA TINCTORIA ROOT 3 [hp_X]/1 mL; GLYCYRRHIZA GLABRA 3 [hp_X]/1 mL; ASTRAGALUS NUTTALLII LEAF 6 [hp_X]/1 mL; SODIUM BORATE 30 [hp_C]/1 mL; OYSTER SHELL CALCIUM CARBONATE, CRUDE 30 [hp_C]/1 mL; WOOD CREOSOTE 30 [hp_C]/1 mL; LYCOPODIUM CLAVATUM SPORE 30 [hp_C]/1 mL; SODIUM PHOSPHATE, DIBASIC, HEPTAHYDRATE 30 [hp_C]/1 mL; NITRIC ACID 30 [hp_C]/1 mL; STRYCHNOS NUX-VOMICA SEED 30 [hp_C]/1 mL; PHOSPHORIC ACID 30 [hp_C]/1 mL; PULSATILLA VULGARIS 30 [hp_C]/1 mL; SEPIA OFFICINALIS JUICE 30 [hp_C]/1 mL; THUJA OCCIDENTALIS LEAFY TWIG 30 [hp_C]/1 mL; CANDIDA ALBICANS 10 [hp_C]/1 mL; CANDIDA ALBICANS 30 [hp_C]/1 mL; CANDIDA ALBICANS 200 [hp_C]/1 mL
INACTIVE INGREDIENTS: WATER; ALCOHOL

CANDIDA HP

ACTIVE INGREDIENT

ACTIVE INGREDIENTS (HPUS*): Echinacea Purpurea MT, Baptisia Tinctoria 3X, Glycyrrhiza Glabra 3X, Astragalus Menziesii 6X, Borax 30C, Calcarea Carbonica 30C, Kreosotum 30C, Lycopodium Clavatum 30C, Natrum Phosphoricum 30C, Nitricum Acidum 30C, Nux Vomica 30C, Phosphoricum Acidum 30C, Pulsatilla 30C, sepia 30C, Thuja Occidentalis 30C, Candida Albicans 10C, 30C, 200C

INDICATIONS AND USAGE

USES: Temporarily relieves headache, diarrhea, constipation, oral thrush, exhaustion, irritability, leucorrhea, itching & redness of female areas, &/or other symptoms related to a candida infection.

WARNING:

Consult a physician for use in children under 12 years of age. IF PREGNANT OR BREAST-FEEDING, ask a health care professional before use. KEEP OUT OF THE REACH OF CHILDREN. In case of overdose (or accidental ingestion) get medical help or contact a Poison Control Center right away.

DOSAGE AND ADMINISTRATION

DIRECTIONS: Adults & children above 12 years: 10 drops orally 3 times daily, or as directed by a health care professional.

OTHER INFORMATION: Tamper Seal: "Sealed for your protection.

Do not use if seal is broken or missing.

REFERENCES

*The letters "HPUS" indicate the components in the product are officially monographed in the Homeopathic Pharmacopeia of the United States.

INACTIVE INGREDIENTS: Purified Water, USP Ethanol Alcohol 20%

QUESTIONS AND COMMENTS?

MFG FOR: Natural Creations / Woodbine, IA / 51579 712.647.2780

LOT:

PURPOSE

USES: Temporarily relieves headache, diarrhea, constipation, oral thrush, exhaustion, irritability, leucorrhea, itching & redness of female areas, &/or other symptoms related to a candida infection.

KEEP OUT OF REACH OF CHILDREN

KEEP OUT OF THE REACH OF CHILDREN. In case of overdose (or accidental ingestion) get medical help or contact a Poison Control Center.

PACKAGE LABEL

NDC: 43406-0011-1

CANDIDA HP

Candida Infection

HOMEOPATHIC

1 fl oz (30 mL) / 20% Ethanol (Alcohol)

UPC: 877730000774